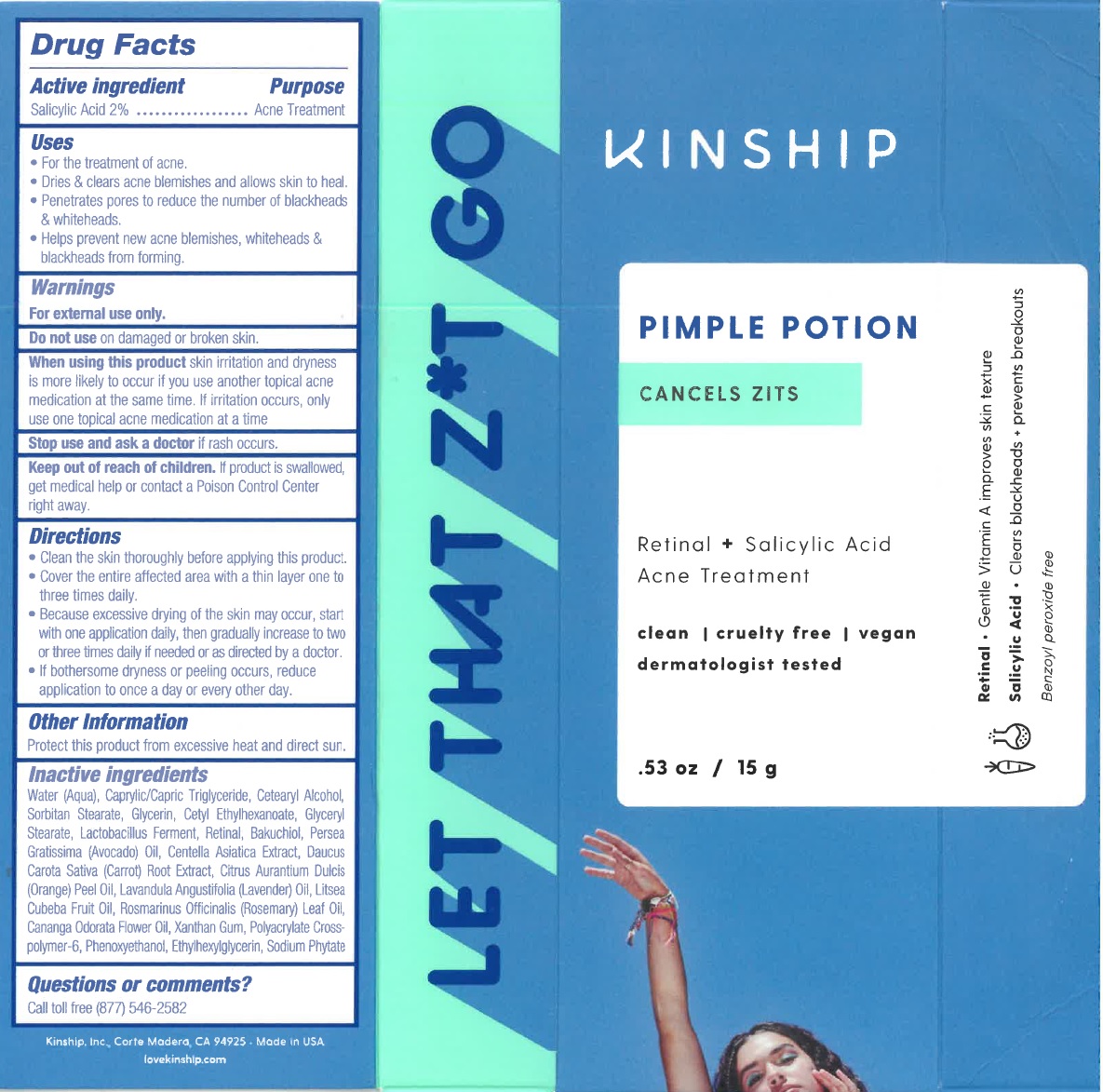 DRUG LABEL: Pimple Potion Retinal Plus Salicylic Acid Acne Treatment
NDC: 62742-4182 | Form: CREAM
Manufacturer: Allure Labs Inc
Category: otc | Type: HUMAN OTC DRUG LABEL
Date: 20191212

ACTIVE INGREDIENTS: SALICYLIC ACID 20 mg/1 g
INACTIVE INGREDIENTS: WATER; MEDIUM-CHAIN TRIGLYCERIDES; CETOSTEARYL ALCOHOL; SORBITAN MONOSTEARATE; GLYCERIN; CETYL ETHYLHEXANOATE; GLYCERYL MONOSTEARATE; LACTOBACILLUS REUTERI; RETINAL, ALL-TRANS; BAKUCHIOL; AVOCADO OIL; CENTELLA ASIATICA WHOLE; CARROT; ORANGE OIL; LAVENDER OIL; LITSEA OIL; ROSEMARY OIL; CANANGA OIL; XANTHAN GUM; AMMONIUM ACRYLOYLDIMETHYLTAURATE, DIMETHYLACRYLAMIDE, LAURYL METHACRYLATE AND LAURETH-4 METHACRYLATE COPOLYMER, TRIMETHYLOLPROPANE TRIACRYLATE CROSSLINKED (45000 MPA.S); PHENOXYETHANOL; ETHYLHEXYLGLYCERIN; PHYTATE SODIUM

DRUG FACTS

Active Ingredient: Salicylic Acid 2%

Purpose: Acne Treatment

Uses:

- For the treatment of acne
- Dries & clears acne blemishes and allow skin to heal.
- Penetrates pores to reduce the number of blackheads and whiteheads.
- Helps prevent new acne blemishes, whiteheads & blackheads from forming.

Warnings: For external use only.

Do not use on damaged or broken skin.

KEEP OUT OF REACH OF CHILDREN

Keep out of the reach of children. If product is swallowed, get medical help or contact a Poison Control Center right away.

When using this product skin irritation and dryness is more likely to occur if you use another topical acne medication at the same time. If irritation occurs, only use one topical acne medication at a time.

Stop use and ask a doctor if rash occurs.

DOSAGE AND ADMINISTRATION

- Clean the skin thoroughly before applying this product.
- Cover the entire affected area with a thin layer one to three times daily.
- Because excessive drying of the skin may occur, start with one application daily, then gradually increase to two to three times daily if needed or as directed by a doctor.
- If bothersome dryness or peeling occurs, reduce application to once a day or every other day.

Other Information: Protect this product from excessive heat and direct sun.

Questions or comments?

Call toll free (877) 546-2582

INACTIVE INGREDIENT

Water (Aqua), Caprylic/Capric Triglyceride, Cetearyl Alcohol, Sorbitan Stearate, Glycerin, Cetyl Ethylhexanoate, Glyceryl Stearate, Lactobacillus Ferment, Retinal, Bakuchiol, Persea Gratissima (Avocado) Oil, Centella Asiatica Extract, Daucus Carota Sativa (Carrrot) Root Extract, Citrus Aurantium Dulcis (Orange) Peel Oil, Lavandula Angustifolia (Lavender) Oil, Litsea Cubeba fruit Oil, Rosmarinus Officinalis (Rosemary) Leaf Oil, Cananga Odorata Flower Oil, Xanthan Gum, Polyacrylate Crosspolymer-6, Phenoxyethanol, Ethylhexylglycerin, Sodium Phytate.

PACKAGE LABEL

Kinship Inc.,

Corte Modera, CA 94925

Made In USA

lovekinship.com